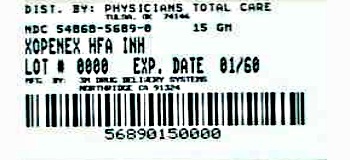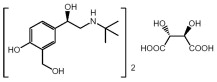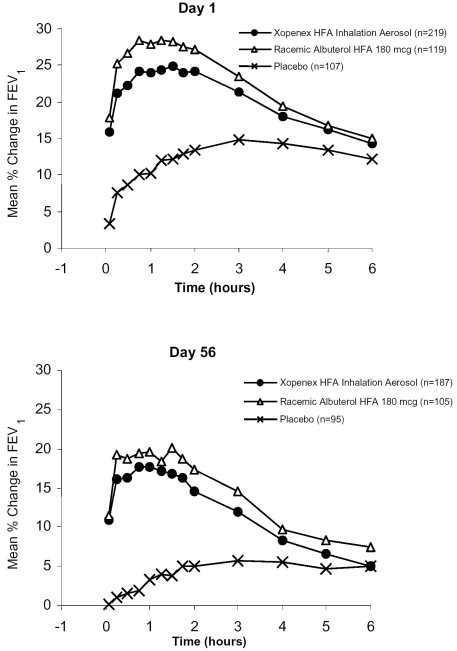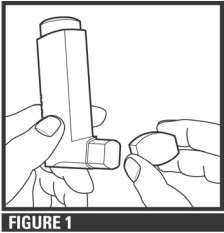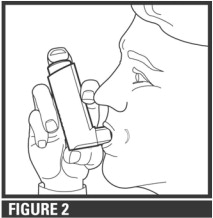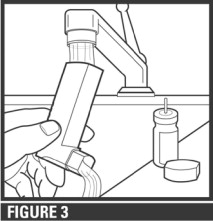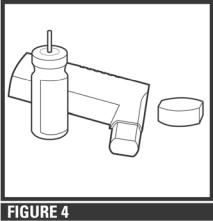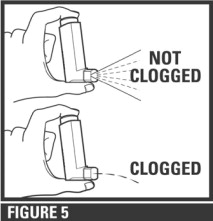 DRUG LABEL: Xopenex HFA
NDC: 54868-5689 | Form: AEROSOL, METERED
Manufacturer: Physicians Total Care, Inc.
Category: prescription | Type: HUMAN PRESCRIPTION DRUG LABEL
Date: 20120507

ACTIVE INGREDIENTS: levalbuterol tartrate 45 ug/1 1
INACTIVE INGREDIENTS: norflurane; Alcohol; Oleic Acid

XOPENEX HFA® (levalbuterol tartrate) Inhalation Aerosol

For Oral Inhalation Only
PRESCRIBING INFORMATION

DESCRIPTION

The active component of XOPENEX HFA (levalbuterol tartrate) Inhalation Aerosol is levalbuterol tartrate, the (R)-enantiomer of albuterol. Levalbuterol tartrate is a relatively selective beta2-adrenergic receptor agonist (see CLINICAL PHARMACOLOGY). Levalbuterol tartrate has the chemical name (R)-α^1-[[(1,1-dimethylethyl)amino]methyl]-4-hydroxy-1,3-benzenedimethanol L-tartrate (2:1 salt), and it has the following chemical structure:

The molecular weight of levalbuterol tartrate is 628.71, and its empirical formula is (C13H21NO3)2 · C4H6O6. It is a white to light-yellow solid, freely soluble in water and very slightly soluble in ethanol.

Levalbuterol tartrate is the generic name for (R)-albuterol tartrate in the United States. XOPENEX HFA Inhalation Aerosol is a pressurized metered-dose aerosol inhaler (MDI), which produces an aerosol for oral inhalation. It contains a suspension of micronized levalbuterol tartrate, propellant HFA-134a (1,1,1,2-tetrafluoroethane), Dehydrated Alcohol USP, and Oleic Acid NF.

The inhaler should be primed by releasing 4 sprays into the air, away from the face, before using it for the first time and when the inhaler has not been used for more than 3 days. After priming with 4 actuations, each actuation delivers 59 mcg of levalbuterol tartrate (equivalent to 45 mcg of levalbuterol free base) from the actuator (or mouthpiece). Each 15 g canister provides 200 actuations (or inhalations) and each 8.4 g canister provides 80 actuations (or inhalations).

This product does not contain chlorofluorocarbons (CFCs).

CLINICAL PHARMACOLOGY

Mechanism of Action: Activation of beta2-adrenergic receptors on airway smooth muscle leads to the activation of adenylate cyclase and to an increase in the intracellular concentration of cyclic-3', 5'-adenosine monophosphate (cyclic AMP). The increase in cyclic AMP is associated with the activation of protein kinase A, which in turn, inhibits the phosphorylation of myosin and lowers intracellular ionic calcium concentrations, resulting in muscle relaxation. Levalbuterol relaxes the smooth muscles of all airways, from the trachea to the terminal bronchioles. Increased cyclic AMP concentrations are also associated with the inhibition of the release of mediators from mast cells in the airways. Levalbuterol acts as a functional antagonist to relax the airway irrespective of the spasmogen involved, thus protecting against all bronchoconstrictor challenges. While it is recognized that beta2-adrenergic receptors are the predominant receptors on bronchial smooth muscle, data indicate that there are beta-receptors in the human heart, 10% to 50% of which are beta2-adrenergic receptors. The precise function of these receptors has not been established (see WARNINGS). However, all beta-adrenergic agonist drugs can produce a significant cardiovascular effect in some patients, as measured by pulse rate, blood pressure, symptoms, and/or electrocardiographic changes.

Preclinical

Results from in vitro studies of binding to human beta-adrenergic receptors demonstrated that levalbuterol has approximately 2-fold greater binding affinity than racemic albuterol and approximately 100-fold greater binding affinity than (S)-albuterol. In guinea pig airways, levalbuterol HCl and racemic albuterol decreased the response to spasmogens (e.g., acetylcholine and histamine), whereas (S)-albuterol was ineffective. These results suggest that the bronchodilatory effects of racemic albuterol are attributable to the (R)-enantiomer.

Intravenous studies in rats with racemic albuterol sulfate have demonstrated that albuterol crosses the blood-brain barrier and reaches brain concentrations amounting to approximately 5.0% of the plasma concentrations. In structures outside the blood-brain barrier (pineal and pituitary glands), racemic albuterol concentrations were found to be 100 times those in the whole brain.

Studies in laboratory animals (minipigs, rodents, and dogs) have demonstrated the occurrence of cardiac arrhythmias and sudden death (with histologic evidence of myocardial necrosis) when beta-agonists and methylxanthines are administered concurrently. The clinical significance of these findings is unknown.

Propellant HFA-134a is devoid of pharmacological activity except at very high doses in animals (380 to 1300 times the maximum human exposure based on comparisons of AUC values), primarily producing ataxia, tremors, dyspnea, or salivation. These are similar to effects produced by the structurally related chlorofluorocarbons (CFCs), which have been used extensively in metered-dose inhalers.

In animals and humans, propellant HFA-134a was found to be rapidly absorbed and rapidly eliminated, with an elimination half-life of 3 to 27 minutes in animals and 5 to 7 minutes in humans. Time to maximum plasma concentration (tmax) and mean residence time are both extremely short, leading to a transient appearance of HFA-134a in the blood with no evidence of accumulation.

Pharmacokinetics

A population pharmacokinetic (PPK) model was developed using plasma concentrations of (R)-albuterol obtained from 632 asthmatic patients aged 4 to 81 years in three large trials. The PPK model-derived pharmacokinetic parameters for (R)-albuterol in pediatric and adolescent/adult patients receiving a 90 mcg dose of XOPENEX HFA (levalbuterol tartrate) Inhalation Aerosol or a 180 mcg dose of racemic albuterol by HFA metered-dose inhaler are presented in Table 1.

These pharmacokinetic data indicate that mean exposure to (R)-albuterol was 13% to 16% less in adult and 30% to 32% less in pediatric patients given XOPENEX HFA Inhalation Aerosol as compared to those given a comparable dose of racemic albuterol. When compared to adult patients, pediatric patients given 90 mcg of levalbuterol have a 17% lower mean exposure to (R)-albuterol.

Table 1: Mean Model-Predicted (R)-Albuterol Pharmacokinetic Parameters
Study Population | Parameter | Treatment
Study Population | Parameter | XOPENEX HFA Inhalation Aerosol | Racemic Albuterol HFA MDI
Adolescent/Adult Patients (≥12 years) | Cmax (ng/mL) | 0.199 | 0.238
Adolescent/Adult Patients (≥12 years) | tmax (hr) | 0.54 | 0.53
Adolescent/Adult Patients (≥12 years) | AUC(0-6) (ng·hr/mL) | 0.695 | 0.798
Pediatric Patients (4-11 years) | Cmax (ng/mL) | 0.163 | 0.238
Pediatric Patients (4-11 years) | tmax (hr) | 0.76 | 0.78
Pediatric Patients (4-11 years) | AUC(0-6) (ng·hr/mL) | 0.579 | 0.828

Metabolism and Elimination

Information available in the published literature suggests that the primary enzyme responsible for the metabolism of albuterol enantiomers in humans is SULT1A3 (sulfotransferase). When racemic albuterol was administered either intravenously or via inhalation after oral charcoal administration, there was a 3- to 4-fold difference in the area under the concentration-time curves between the (R)- and (S)-albuterol enantiomers, with (S)-albuterol concentrations being consistently higher. However, without charcoal pretreatment, after either oral or inhalation administration the differences were 8- to 24-fold, suggesting that that (R)-albuterol is preferentially metabolized in the gastrointestinal tract, presumably by SULT1A3.

The primary route of elimination of albuterol enantiomers is through renal excretion (80% to 100%) of either the parent compound or the primary metabolite. Less than 20% of the drug is detected in the feces. Following intravenous administration of racemic albuterol, between 25% and 46% of the (R)-albuterol fraction of the dose was excreted as unchanged (R)-albuterol in the urine.

Special Populations

Hepatic Impairment: The effect of hepatic impairment on the pharmacokinetics of XOPENEX HFA Inhalation Aerosol has not been evaluated.

Renal Impairment: The effect of renal impairment on the pharmacokinetics of racemic albuterol was evaluated in 5 subjects with creatinine clearance of 7 to 53 mL/min, and the results were compared with those from healthy volunteers. Renal disease had no effect on the half-life, but there was a 67% decline in racemic albuterol clearance. Caution should be used when administering high doses of XOPENEX HFA Inhalation Aerosol to patients with renal impairment.

Clinical Trials

Adults and Adolescents: The efficacy and safety of XOPENEX HFA Inhalation Aerosol were established in two 8-week, multicenter, randomized, double-blind, active- and placebo-controlled trials in 748 adults and adolescents with asthma between the ages of 12 and 81 years. In these two trials, XOPENEX HFA Inhalation Aerosol (403 patients) was compared to an HFA-134a placebo MDI (166 patients), and the trials included a marketed albuterol HFA-134a MDI (179 patients) as an active control. Serial forced expiratory volume in 1 second (FEV1) measurements demonstrated that 90 mcg (2 inhalations) of XOPENEX HFA Inhalation Aerosol produced significantly greater improvement in FEV1 over the pretreatment value than placebo. The results from one of the trials are shown in Figure 1 as the mean percent change in FEV1 from test-day baseline at Day 1 (n=445) and Day 56 (n=387). The results from the second trial were similar.

Figure 1: Percent Change in FEV1 from Test-Day Baseline in Adults and Adolescents Aged 12 to 81 Years at Day 1 and Day 56

For XOPENEX HFA Inhalation Aerosol on Day 1, the median time to onset of a 15% increase in FEV1 ranged from 5.5 to 10.2 minutes and the median time to peak effect ranged from 76 to 78 minutes. In the responder population, on Day 1 the median duration of effect as measured by a 15% increase in FEV1 was 3 to 4 hours, with duration of effect in some patients of up to 6 hours.

Pediatrics: The efficacy and safety of XOPENEX HFA Inhalation Aerosol in children were established in a 4-week, multicenter, randomized, double-blind, active- and placebo-controlled trial in 150 pediatric patients with asthma between the ages of 4 and 11 years. In this trial, XOPENEX HFA Inhalation Aerosol (76 patients) was compared to a placebo HFA-134a MDI (35 patients), and the trial included a marketed albuterol HFA-134a MDI (39 patients) as an active control. Serial FEV1 measurements demonstrated that 90 mcg (2 inhalations) of XOPENEX HFA Inhalation Aerosol produced significantly greater improvement in FEV1 over the pretreatment value than placebo and were consistent with the efficacy findings in the adult studies.

For XOPENEX HFA Inhalation Aerosol, on Day 1 the median time to onset of a 15% increase in FEV1 was 4.5 minutes and the median time to peak effect was 77 minutes. In the responder population, the median duration of effect as measured by a 15% increase in FEV1 was 3 hours, with a duration of effect in some pediatric patients of up to 6 hours.

INDICATIONS AND USAGE

XOPENEX HFA (levalbuterol tartrate) Inhalation Aerosol is indicated for the treatment or prevention of bronchospasm in adults, adolescents, and children 4 years of age and older with reversible obstructive airway disease.

CONTRAINDICATIONS

XOPENEX HFA (levalbuterol tartrate) Inhalation Aerosol is contraindicated in patients with a history of hypersensitivity to levalbuterol, racemic albuterol, or any other component of XOPENEX HFA Inhalation Aerosol.

WARNINGS

1. Paradoxical Bronchospasm: Like other inhaled beta-adrenergic agonists, XOPENEX HFA Inhalation Aerosol can produce paradoxical bronchospasm, which may be life-threatening. If paradoxical bronchospasm occurs, XOPENEX HFA (levalbuterol tartrate) Inhalation Aerosol should be discontinued immediately and alternative therapy instituted. It should be recognized that paradoxical bronchospasm, when associated with inhaled formulations, frequently occurs with the first use of a new canister.
2. Deterioration of Asthma: Asthma may deteriorate acutely over a period of hours or chronically over several days or longer. If the patient needs more doses of XOPENEX HFA Inhalation Aerosol than usual, this may be a marker of destabilization of asthma and requires reevaluation of the patient and treatment regimen, giving special consideration to the possible need for anti-inflammatory treatment, e.g., corticosteroids.
3. Use of Anti-Inflammatory Agents: The use of a beta-adrenergic agonist alone may not be adequate to control asthma in many patients. Early consideration should be given to adding anti-inflammatory agents, e.g., corticosteroids, to the therapeutic regimen.
4. Cardiovascular Effects: XOPENEX HFA Inhalation Aerosol, like other beta-adrenergic agonists, can produce clinically significant cardiovascular effects in some patients, as measured by heart rate, blood pressure, and/or symptoms. Although such effects are uncommon after administration of XOPENEX HFA Inhalation Aerosol at recommended doses, if they occur, the drug may need to be discontinued. In addition, beta-agonists have been reported to produce electrocardiogram (ECG) changes, such as flattening of the T wave, prolongation of the QTc interval, and ST segment depression. The clinical significance of these findings is unknown. Therefore, XOPENEX HFA Inhalation Aerosol, like all sympathomimetic amines, should be used with caution in patients with cardiovascular disorders, especially coronary insufficiency, cardiac arrhythmias, and hypertension.
5. Do Not Exceed Recommended Dose: Fatalities have been reported in association with excessive use of inhaled sympathomimetic drugs in patients with asthma. The exact cause of death is unknown, but cardiac arrest following an unexpected development of a severe acute asthmatic crisis and subsequent hypoxia is suspected.
6. Immediate Hypersensitivity Reactions: Immediate hypersensitivity reactions may occur after administration of racemic albuterol, as demonstrated by rare cases of urticaria, angioedema, rash, bronchospasm, anaphylaxis, and oropharyngeal edema. The potential for hypersensitivity must be considered in the clinical evaluation of patients who experience immediate hypersensitivity reactions while receiving XOPENEX HFA Inhalation Aerosol.

PRECAUTIONS

General

XOPENEX HFA (levalbuterol tartrate) Inhalation Aerosol, like all sympathomimetic amines, should be used with caution in patients with cardiovascular disorders, especially coronary insufficiency, hypertension, and cardiac arrhythmias; in patients with convulsive disorders, hyperthyroidism, or diabetes mellitus; and in patients who are unusually responsive to sympathomimetic amines. Clinically significant changes in systolic and diastolic blood pressure have been seen in individual patients and could be expected to occur in some patients after the use of any beta-adrenergic bronchodilator.

Large doses of intravenous racemic albuterol have been reported to aggravate preexisting diabetes mellitus and ketoacidosis. As with other beta-adrenergic agonist medications, XOPENEX HFA Inhalation Aerosol may produce significant hypokalemia in some patients, possibly through intracellular shunting, which has the potential to produce adverse cardiovascular effects. The decrease is usually transient, not requiring supplementation.

Information for Patients

See illustrated Patient's Instructions for Use. SHAKE WELL BEFORE USING. Patients should be given the following information: It is recommended to prime the inhaler before using for the first time and in cases where the inhaler has not been used for more than 3 days by releasing 4 test sprays into the air, away from the face.

KEEPING THE PLASTIC ACTUATOR CLEAN IS VERY IMPORTANT TO PREVENT MEDICATION BUILD-UP AND BLOCKAGE. THE ACTUATOR SHOULD BE WASHED, SHAKEN TO REMOVE EXCESS WATER, AND AIR-DRIED THOROUGHLY AT LEAST ONCE A WEEK. THE INHALER MAY CEASE TO DELIVER MEDICATION IF NOT PROPERLY CLEANED.

The actuator should be cleaned (with the canister removed) by running warm water through the top and bottom for 30 seconds at least once a week. Do not attempt to clean the metal canister or allow the metal canister to become wet. Never immerse the metal canister in water. The actuator must be shaken to remove excess water, then air-dried thoroughly (such as overnight). Blockage from medication build-up or improper medication delivery may result from failure to clean and thoroughly air-dry the actuator.

If the actuator becomes blocked (little or no medication coming out of the mouthpiece), the blockage may be removed by washing the actuator as described above.

If it is necessary to use the inhaler before it is completely dry, shake excess water off the plastic actuator, replace canister, shake well, test-spray twice away from face, and take the prescribed dose. After such use, the actuator should be rewashed and allowed to air-dry thoroughly.

The action of XOPENEX HFA Inhalation Aerosol should last for 4 to 6 hours. XOPENEX HFA Inhalation Aerosol should not be used more frequently than recommended. Do not increase the dose or frequency of doses of XOPENEX HFA Inhalation Aerosol without consulting your physician. If you find that treatment with XOPENEX HFA Inhalation Aerosol becomes less effective for symptomatic relief, your symptoms become worse, and/or you need to use the product more frequently than usual, you should seek medical attention immediately. While you are using XOPENEX HFA Inhalation Aerosol, other inhaled drugs and asthma medication should be taken only as directed by your physician.

Common adverse effects of treatment with inhaled beta-agonists include palpitations, chest pain, rapid heart rate, tremor, and nervousness. If you are pregnant or nursing, contact your physician about use of XOPENEX HFA Inhalation Aerosol. Effective and safe use of XOPENEX HFA Inhalation Aerosol includes an understanding of the way that it should be administered.

Use XOPENEX HFA Inhalation Aerosol only with the actuator supplied with the product. Discard the canister after 200 sprays have been used from the 15 g canister or after 80 sprays have been used from the 8.4 g canister. Never immerse the canister in water to determine how full the canister is (“float test”).

In general, the technique for administering XOPENEX HFA Inhalation Aerosol to children is similar to that for adults. Children should use XOPENEX HFA Inhalation Aerosol under adult supervision, as instructed by the patient's physician. (See Patient's Instructions for Use.)

Drug Interactions

Other short-acting sympathomimetic aerosol bronchodilators or epinephrine should be used with caution with XOPENEX HFA Inhalation Aerosol. If additional adrenergic drugs are to be administered by any route, they should be used with caution to avoid deleterious cardiovascular effects.

1. Beta-blockers: Beta-adrenergic receptor blocking agents not only block the pulmonary effect of beta-adrenergic agonists, such as XOPENEX HFA Inhalation Aerosol, but may produce severe bronchospasm in asthmatic patients. Therefore, patients with asthma should not normally be treated with beta-blockers. However, under certain circumstances, e.g., as prophylaxis after myocardial infarction, there may be no acceptable alternatives to the use of beta-adrenergic blocking agents in patients with asthma. In this setting, cardioselective beta-blockers should be considered, although they should be administered with caution.
2. Diuretics: The ECG changes and/or hypokalemia that may result from the administration of non–potassium-sparing diuretics (such as loop and thiazide diuretics) can be acutely worsened by beta-agonists, especially when the recommended dose of the beta-agonist is exceeded. Although the clinical significance of these effects is not known, caution is advised in the coadministration of beta-agonists with non–potassium-sparing diuretics.
3. Digoxin: Mean decreases of 16% to 22% in serum digoxin levels were demonstrated after single-dose intravenous and oral administration of racemic albuterol, respectively, to normal volunteers who had received digoxin for 10 days. The clinical significance of these findings for patients with obstructive airway disease who are receiving XOPENEX HFA Inhalation Aerosol and digoxin on a chronic basis is unclear. Nevertheless, it would be prudent to carefully evaluate the serum digoxin levels in patients who are currently receiving digoxin and XOPENEX HFA Inhalation Aerosol.
4. Monoamine Oxidase Inhibitors or Tricyclic Antidepressants: XOPENEX HFA Inhalation Aerosol should be administered with extreme caution to patients being treated with monoamine oxidase inhibitors or tricyclic antidepressants, or within 2 weeks of discontinuation of such agents, because the action of albuterol on the vascular system may be potentiated.

Carcinogenesis, Mutagenesis, and Impairment of Fertility

No carcinogenesis or impairment of fertility studies have been carried out with levalbuterol tartrate. However, racemic albuterol sulfate has been evaluated for its carcinogenic potential and ability to impair fertility.

In a 2-year study in Sprague-Dawley rats, racemic albuterol sulfate caused a significant dose-related increase in the incidence of benign leiomyomas of the mesovarium at, and above, dietary doses of 2 mg/kg/day (approximately 30 times the maximum recommended daily inhalation dose of levalbuterol tartrate for adults on a mg/m^2 basis and approximately 15 times the maximum recommended daily inhalation dose of levalbuterol tartrate for children on a mg/m^2 basis). In another study, this effect was blocked by the coadministration of propranolol, a nonselective beta-adrenergic antagonist. In an 18-month study in CD-1 mice, racemic albuterol sulfate showed no evidence of tumorigenicity at dietary doses up to 500 mg/kg/day (approximately 3800 times the maximum recommended daily inhalation dose of levalbuterol tartrate for adults on a mg/m^2 basis and approximately 1800 times the maximum recommended daily inhalation dose of levalbuterol tartrate for children on a mg/m^2 basis). In a 22-month study in the Golden hamster, racemic albuterol sulfate showed no evidence of tumorigenicity at dietary doses up to 50 mg/kg/day (approximately 500 times the maximum recommended daily inhalation dose of levalbuterol tartrate for adults on a mg/m^2 basis and approximately 240 times the maximum recommended daily inhalation dose of levalbuterol tartrate for children on a mg/m^2 basis).

Levalbuterol HCl was not mutagenic in the Ames test or the CHO/HPRT Mammalian Forward Gene Mutation Assay. Levalbuterol HCl was not clastogenic in the in vivo micronucleus test in mouse bone marrow. Racemic albuterol sulfate was negative in an in vitro chromosomal aberration assay in CHO cell cultures.

Reproduction studies in rats using racemic albuterol sulfate demonstrated no evidence of impaired fertility at oral doses up to 50 mg/kg/day (approximately 750 times the maximum recommended daily inhalation dose of levalbuterol tartrate for adults on a mg/m^2 basis).

Teratogenic Effects - Pregnancy Category C

A reproduction study in New Zealand White rabbits demonstrated that levalbuterol HCl was not teratogenic when administered orally at doses up to 25 mg/kg/day (approximately 750 times the maximum recommended daily inhalation dose of levalbuterol tartrate for adults on a mg/m^2 basis).

However, racemic albuterol sulfate has been shown to be teratogenic in mice and rabbits. A study in CD-1 mice given racemic albuterol sulfate subcutaneously showed cleft palate formation in 5 of 111 (4.5%) fetuses at 0.25 mg/kg/day (approximately 2 times the maximum recommended daily inhalation dose of levalbuterol tartrate for adults on a mg/m^2 basis) and in 10 of 108 (9.3%) fetuses at 2.5 mg/kg/day (approximately 20 times the maximum recommended daily inhalation dose of levalbuterol tartrate for adults on a mg/m^2 basis). The drug did not induce cleft palate formation when administered subcutaneously at a dose of 0.025 mg/kg/day (less than the maximum recommended daily inhalation dose of levalbuterol tartrate for adults on a mg/m^2 basis). Cleft palate also occurred in 22 of 72 (30.5%) fetuses from females treated subcutaneously with 2.5 mg/kg/day of isoproterenol (positive control).

A reproduction study in Stride Dutch rabbits revealed cranioschisis in 7 of 19 (37%) fetuses when racemic albuterol sulfate was administered orally at a dose of 50 mg/kg/day (approximately 1500 times the maximum recommended daily inhalation dose of levalbuterol tartrate for adults on a mg/m^2 basis).

A study in which pregnant rats were dosed with radiolabeled racemic albuterol sulfate demonstrated that drug-related material is transferred from the maternal circulation to the fetus.

There are no adequate and well-controlled studies of XOPENEX HFA Inhalation Aerosol in pregnant women. Because animal reproduction studies are not always predictive of human response, XOPENEX HFA Inhalation Aerosol should be used during pregnancy only if the potential benefit justifies the potential risk to the fetus.

During marketing experience of racemic albuterol, various congenital anomalies, including cleft palate and limb defects, have been rarely reported in the offspring of patients being treated with racemic albuterol. Some of the mothers were taking multiple medications during their pregnancies. No consistent pattern of defects can be discerned, and a relationship between racemic albuterol use and congenital anomalies has not been established.

Use in Labor and Delivery

Because of the potential for beta-adrenergic agonists to interfere with uterine contractility, the use of XOPENEX HFA Inhalation Aerosol for the treatment of bronchospasm during labor should be restricted to those patients in whom the benefits clearly outweigh the risk.

Tocolysis

XOPENEX HFA Inhalation Aerosol has not been approved for the management of preterm labor. The benefit:risk ratio when levalbuterol tartrate is administered for tocolysis has not been established. Serious adverse reactions, including maternal pulmonary edema, have been reported during or following treatment of premature labor with beta2-agonists, including racemic albuterol.

Nursing Mothers

Plasma concentrations of levalbuterol after inhalation of therapeutic doses are very low in humans. It is not known whether levalbuterol is excreted in human milk.

Because of the potential for tumorigenicity shown for racemic albuterol in animal studies and the lack of experience with the use of XOPENEX HFA Inhalation Aerosol by nursing mothers, a decision should be made whether to discontinue nursing or to discontinue the drug, taking into account the importance of the drug to the mother. Caution should be exercised when XOPENEX HFA Inhalation Aerosol is administered to a nursing woman.

Pediatrics

The safety and efficacy of XOPENEX HFA Inhalation Aerosol have been established in pediatric patients 4 years of age and older in an adequate and well-controlled clinical trial (see Clinical Trials). Use of XOPENEX HFA Inhalation Aerosol in children is also supported by evidence from adequate and well-controlled studies of XOPENEX HFA Inhalation Aerosol in adults, considering that the pathophysiology, systemic exposure of the drug, and clinical profile in pediatric and adult patients are substantially similar. Safety and effectiveness of XOPENEX HFA Inhalation Aerosol in pediatric patients below the age of 4 years have not been established.

Geriatrics

Clinical studies of XOPENEX HFA Inhalation Aerosol did not include sufficient numbers of subjects aged 65 and older to determine whether they respond differently from younger subjects. Other reported clinical experience has not identified differences in responses between the elderly and younger patients. In general, dose selection for an elderly patient should be cautious, usually starting at the low end of the dosing range, reflecting the greater frequency of decreased hepatic, renal, or cardiac function, and of concomitant diseases or other drug therapy.

Albuterol is known to be substantially excreted by the kidney, and the risk of toxic reactions may be greater in patients with impaired renal function. Because elderly patients are more likely to have decreased renal function, care should be taken in dose selection, and it may be useful to monitor renal function.

ADVERSE REACTIONS

Adverse event information concerning XOPENEX HFA (levalbuterol tartrate) Inhalation Aerosol in adults and adolescents is derived from two 8-week, multicenter, randomized, double-blind, active- and placebo-controlled trials in 748 adult and adolescent patients with asthma that compared XOPENEX HFA Inhalation Aerosol, a marketed albuterol HFA inhaler, and an HFA-134a placebo inhaler. Table 2 lists the incidence of all adverse events (whether considered by the investigator to be related or unrelated to drug) from these trials that occurred at a rate of 2% or greater in the group treated with XOPENEX HFA Inhalation Aerosol and more frequently than in the HFA-134a placebo inhaler group.

Table 2: Adverse Event Incidence (% of Patients) in Two 8-Week Clinical Trials in Adults and Adolescents ≥ 12 Years of Age*
Body System Preferred Term | XOPENEX HFA Inhalation Aerosol 90 mcg (n=403) | Racemic Albuterol HFA 180 mcg (n=179) | Placebo (n=166)
Body as a Whole
Pain | 4.0 | 3.4 | 3.6
Central Nervous System
Dizziness | 2.7 | 0.6 | 1.8
Respiratory System
Asthma | 9.4 | 7.3 | 6.0
Pharyngitis | 7.9 | 2.2 | 2.4
Rhinitis | 7.4 | 2.2 | 3.0
* This table includes all adverse events (whether considered by the investigator to be related or unrelated to drug) from these trials that occurred at a rate of 2% or greater in the group treated with XOPENEX HFA Inhalation Aerosol and more frequently than in the HFA-134a placebo inhaler group.

Adverse events reported by less than 2% and at least 2 or more of the adolescent and adult patients receiving XOPENEX HFA Inhalation Aerosol and by a greater proportion than receiving HFA-134a placebo inhaler include cyst, flu syndrome, viral infection, constipation, gastroenteritis, myalgia, hypertension, epistaxis, lung disorder, acne, herpes simplex, conjunctivitis, ear pain, dysmenorrhea, hematuria, and vaginal moniliasis. There were no significant laboratory abnormalities observed in these studies.

Adverse event information concerning XOPENEX HFA Inhalation Aerosol in children is derived from a 4-week, randomized, double-blind trial of XOPENEX HFA Inhalation Aerosol, a marketed albuterol HFA inhaler, and an HFA-134a placebo inhaler in 150 children aged 4 to 11 years with asthma. Table 3 lists the adverse events reported for XOPENEX HFA Inhalation Aerosol in children at a rate of 2% or greater and more frequently than for placebo.

Table 3: Adverse Event Incidence (% of Patients) in a 4-Week Trial in Children Aged 4-11 Years*
Body System Preferred Term | XOPENEX HFA Inhalation Aerosol 90 mcg (n=76) | Racemic Albuterol HFA 180 mcg (n=39) | Placebo (n=35)
Body as a Whole
Accidental injury | 9.2 | 10.3 | 5.7
Digestive System
Vomiting | 10.5 | 7.7 | 5.7
Respiratory System
Bronchitis | 2.6 | 0 | 0
Pharyngitis | 6.6 | 12.8 | 5.7
* This table includes all adverse events (whether considered by the investigator to be related or unrelated to drug) from the trial that occurred at a rate of 2% or greater in the group treated with XOPENEX HFA Inhalation Aerosol and more frequently than in the HFA-134a placebo inhaler group.

The incidence of systemic beta-adrenergic adverse effects (e.g., tremor, nervousness) was low and comparable across all treatment groups, including placebo.

Postmarketing

In addition to the adverse events reported in clinical trials, the following adverse events have been observed in postapproval use of levalbuterol inhalation solution. These events have been chosen for inclusion due to their seriousness, their frequency of reporting, or their likely beta-mediated mechanism: angioedema, anaphylaxis, arrhythmias (including atrial fibrillation, supraventricular tachycardia, extrasystoles), asthma, chest pain, cough increased, dyspnea, nausea, nervousness, rash, tachycardia, tremor, urticaria. Because these events have been reported spontaneously from a population of unknown size, estimates of frequency cannot be made.

In addition, XOPENEX HFA Inhalation Aerosol, like other sympathomimetic agents, can cause adverse reactions such as hypertension, angina, vertigo, central nervous system stimulation, sleeplessness, headache, and drying or irritation of the oropharynx.

OVERDOSAGE

The expected symptoms with overdosage are those of excessive beta-adrenergic receptor stimulation and/or occurrence or exaggeration of any of the symptoms listed under ADVERSE REACTIONS, e.g., seizures, angina, hypertension or hypotension, tachycardia with rates up to 200 beats/minute, arrhythmias, nervousness, headache, tremor, dry mouth, palpitation, nausea, dizziness, fatigue, malaise, and sleeplessness. Hypokalemia also may occur. As with all sympathomimetic medications, cardiac arrest and even death may be associated with the abuse of XOPENEX HFA (levalbuterol tartrate) Inhalation Aerosol. Treatment consists of discontinuation of XOPENEX HFA Inhalation Aerosol together with appropriate symptomatic therapy. The judicious use of a cardioselective beta-receptor blocker may be considered, bearing in mind that such medication can produce bronchospasm. There is insufficient evidence to determine if dialysis is beneficial for overdosage of XOPENEX HFA Inhalation Aerosol.

Following intravenous administration in mice, the median lethal levalbuterol HCl dose was approximately 66 mg/kg (approximately 500 times the maximum recommended daily inhalation dose of levalbuterol tartrate for adults on a mg/m^2 basis and approximately 230 times the maximum recommended daily inhalation dose of levalbuterol tartrate for pediatric patients on a mg/m^2 basis). Following intravenous administration in rats, the median lethal levalbuterol HCl dose was approximately 60 mg/kg (approximately 900 times the maximum recommended daily inhalation dose of levalbuterol tartrate for adults on a mg/m^2 basis and approximately 430 times the maximum recommended daily inhalation dose of levalbuterol tartrate for children on a mg/m^2 basis). The inhalation median lethal dose has not been determined in animals. In dogs, inhaled doses of levalbuterol HCl up to 2.73 mg/kg (approximately 140 times the maximum recommended daily inhalation dose of levalbuterol tartrate for adults on a mg/m^2 basis and approximately 65 times the maximum recommended daily inhalation dose of levalbuterol tartrate for children on a mg/m^2 basis) were tolerated without animal deaths.

DOSAGE AND ADMINISTRATION

Adult and Pediatric Asthma: For treatment of acute episodes of bronchospasm or prevention of asthmatic symptoms, the usual dosage of XOPENEX HFA (levalbuterol tartrate) Inhalation Aerosol for adults and children 4 years of age and older is 2 inhalations (90 mcg) repeated every 4 to 6 hours; in some patients, 1 inhalation every 4 hours may be sufficient. More frequent administration or a larger number of inhalations is not routinely recommended. It is recommended to prime the inhaler before using for the first time and in cases where the inhaler has not been used for more than 3 days by releasing 4 test sprays into the air, away from the face.

If a previously effective dosage regimen fails to provide the usual response, this may be a marker of destabilization of asthma and requires reevaluation of the patient and the treatment regimen, giving special consideration to the possible need for anti-inflammatory treatment, e.g., corticosteroids.

Cleaning: To maintain proper use of this product, it is critical that the actuator be washed and dried thoroughly at least once a week. The inhaler may cease to deliver medication if not properly cleaned and dried thoroughly. See Information for Patients. Keeping the plastic actuator clean is very important to prevent medication build-up and blockage. If the actuator becomes blocked with drug, washing the actuator will remove the blockage.

HOW SUPPLIED

XOPENEX HFA (levalbuterol tartrate) Inhalation Aerosol is supplied as a pressurized aluminum canister in a box (NDC 54868-5689-0). The canister is labeled with a net weight of 15 g and contains 200 metered actuations (or inhalations), respectively. Each canister is supplied with a blue plastic actuator (or mouthpiece), a red mouthpiece cap, and patient's instructions.

SHAKE WELL BEFORE USING. Store between 20° and 25°C (68° and 77°F; see USP controlled room temperature). Protect from freezing temperatures and direct sunlight. Store inhaler with the actuator (or mouthpiece) down. Avoid spraying in eyes. Contents under pressure. Do not puncture or incinerate. Exposure to temperatures above 120°F may cause bursting. Keep out of reach of children.

The blue actuator supplied with XOPENEX HFA Inhalation Aerosol should not be used with any other product canisters. Actuators from other products should not be used with a XOPENEX HFA Inhalation Aerosol canister. The correct amount of medication in each actuation cannot be assured after 200 actuations from the 15 g canister or 80 actuations from the 8.4 g canister, even though the canister is not completely empty. The canister should be discarded when 200 actuations have been used from the 15 g canister or 80 actuations have been used from the 8.4 g canister.

XOPENEX HFA Inhalation Aerosol does not contain chlorofluorocarbons (CFCs) as the propellant.

Rx only.

Manufactured for:
Sepracor Inc.
Marlborough, MA 01752 USA
by 3M Drug Delivery Systems
Northridge, CA 91324-3213

For customer service, call 1-888-394-7377.
To report adverse events, call 1-877-737-7226.
For medical information, call 1-800-739-0565.

June 2009

900874R05

Additional barcode labeling by:
Physicians Total Care, Inc.
Tulsa, Oklahoma 74146

PHARMACIST — DETACH HERE AND GIVE INSTRUCTIONS TO PATIENT.

-----------------------------------------------------------------------------------------------------------

Patient's Instructions For Use

XOPENEX HFA® (levalbuterol tartrate) Inhalation Aerosol

Before using your XOPENEX HFA (levalbuterol tartrate) Inhalation Aerosol, read the complete instructions carefully.

ABOUT XOPENEX HFA INHALATION AEROSOL

Use only as directed by a doctor. Children should use XOPENEX HFA Inhalation Aerosol under adult supervision, as instructed by the patient's doctor.

XOPENEX HFA Inhalation Aerosol is a pressurized metered-dose inhaler that produces an aerosol for oral inhalation. XOPENEX HFA Inhalation Aerosol does not contain chlorofluorocarbons (CFCs).

The blue actuator (or mouthpiece) supplied with XOPENEX HFA Inhalation Aerosol should not be used with any other product canisters. Actuators from other products should not be used with a XOPENEX HFA Inhalation Aerosol canister.

HOW TO USE YOUR XOPENEX HFA INHALATION AEROSOL

1. SHAKE THE INHALER WELL immediately before each use.
2. REMOVE THE CAP FROM THE ACTUATOR (OR MOUTHPIECE) (see Figure 1). Inspect the actuator for the presence of foreign objects and make sure that the canister is seated in the actuator before each use.
  PRIMING: Priming at specified times is important for the proper delivery of your medication. SHAKE THE INHALER WELL; then prime XOPENEX HFA Inhalation Aerosol by releasing 4 test sprays into the air, away from your face, before using for the first time and when the inhaler has not been used for more than 3 days.
3. BREATHE OUT FULLY THROUGH YOUR MOUTH, expelling as much air from your lungs as possible. Place the mouthpiece fully into your mouth, holding the inhaler in the mouthpiece-down position (see Figure 2) and closing your lips around it.
4. WHILE BREATHING IN DEEPLY AND SLOWLY THROUGH YOUR MOUTH, FULLY DEPRESS THE TOP OF THE METAL CANISTER with your middle finger as shown in Figure 2. Immediately after the puff is delivered, release your finger from the canister and remove the inhaler from your mouth.
5. HOLD YOUR BREATH FOR 10 SECONDS, IF POSSIBLE.
6. If your doctor has prescribed more than a single inhalation/puff, wait 1 minute between inhalations. Then, SHAKE THE INHALER WELL and repeat steps 3 through 5.
7. REPLACE THE CAP ON THE MOUTHPIECE AFTER EACH USE.
8. CLEAN THE ACTUATOR OR MOUTHPIECE AT LEAST ONCE A WEEK. See CLEANING YOUR XOPENEX HFA INHALATION AEROSOL for cleaning instructions.
9. DISCARD THE CANISTER AFTER YOU HAVE USED EITHER 200 INHALATIONS FROM THE 15 g CANISTER OR 80 INHALATIONS FROM THE 8.4 g CANISTER. The correct amount of medicine in each inhalation cannot be assured after 200 sprays from the 15 g canister or 80 sprays from the 8.4 g canister, even though the canister is not completely empty. Never immerse the canister in water to determine how full the canister is (“float test”). Before you reach either 200 sprays or 80 sprays, you should consult your doctor to determine whether a refill is needed. Just as you should not take extra doses without consulting your doctor, you also should not stop using XOPENEX HFA Inhalation Aerosol without consulting your doctor.

CLEANING YOUR XOPENEX HFA INHALATION AEROSOL

KEEPING THE BLUE PLASTIC ACTUATOR (OR MOUTHPIECE) CLEAN IS VERY IMPORTANT TO PREVENT MEDICINE BLOCKAGE. THE ACTUATOR SHOULD BE WASHED, SHAKEN TO REMOVE EXCESS WATER, AND AIR-DRIED THOROUGHLY AT LEAST ONCE A WEEK. THE INHALER MAY STOP WORKING IF NOT PROPERLY CLEANED.

ROUTINE CLEANING INSTRUCTIONS:

Step 1. To clean the blue plastic actuator (or mouthpiece), remove the canister and red mouthpiece cap.
Step 2. Wash the actuator through the top and bottom with warm running water for 30 seconds at least once a week (see Figure 3).
  Do not clean the metal canister or allow the metal canister to become wet. Never immerse the metal canister in water.
Step 3. To dry, shake off excess water and let the actuator air-dry thoroughly, such as overnight (see Figure 4).
Step 4. When the actuator is dry, replace the canister and the mouthpiece cap; make sure the canister is fully and firmly inserted into the actuator. Blockage from medicine build-up is more likely to occur if the actuator is not allowed to air-dry thoroughly.

IF YOUR ACTUATOR BECOMES BLOCKED (little or no medicine coming out of the mouthpiece, see Figure 5), wash your actuator as described in Steps 1 and 2 and air-dry thoroughly as described in Step 3.

IF YOU NEED TO USE YOUR INHALER BEFORE THE PLASTIC ACTUATOR IS COMPLETELY DRY, SHAKE EXCESS WATER off the actuator, replace the canister, shake well, and test-spray twice into the air, away from your face, to remove most of the water remaining in the actuator. Then take your dose as prescribed. After such use, rewash the actuator and air-dry it thoroughly as described in Steps 1 through 3.

ADDITIONAL INFORMATION ABOUT XOPENEX HFA INHALATION AEROSOL

DOSAGE: Use only as directed by your doctor.

WARNINGS: The action of XOPENEX HFA Inhalation Aerosol should last for 4 to 6 hours. XOPENEX HFA Inhalation Aerosol should not be used more frequently than recommended. Do not increase the dose or frequency of doses of XOPENEX HFA Inhalation Aerosol without consulting your physician. If you find that treatment with XOPENEX HFA Inhalation Aerosol becomes less effective for symptomatic relief, your symptoms become worse, and/or you need to use the product more frequently than usual, you should seek medical attention immediately. While you are using XOPENEX HFA Inhalation Aerosol, other inhaled drugs and asthma medication should be taken only as directed by your physician.

Common adverse effects include palpitations, chest pain, rapid heart rate, tremor, and nervousness. If you are pregnant or nursing, contact your physician about the use of XOPENEX HFA Inhalation Aerosol. Effective and safe use of XOPENEX HFA Inhalation Aerosol includes an understanding of the way that it should be administered. In general, the technique for administering XOPENEX HFA Inhalation Aerosol to children is similar to that for adults. Children should use XOPENEX HFA Inhalation Aerosol under adult supervision, as instructed by the patient's physician.

Storage: Store canister between 20° and 25°C (68° and 77°F). Protect from freezing temperatures and direct sunlight. Store inhaler with the actuator (or mouthpiece) down. Contents under pressure. Do not puncture or incinerate. Exposure to temperatures above 120°F may cause bursting. Avoid spraying in eyes. Keep out of reach of children.

CFC-Free: XOPENEX HFA Inhalation Aerosol does not contain chlorofluorocarbons (CFCs). Instead, the inhaler contains a hydrofluoroalkane (HFA-134a) as the propellant.

Manufactured for:
Sepracor Inc.
Marlborough, MA 01752 USA
by 3M Drug Delivery Systems
Northridge, CA 91324-3213

For customer service, call 1-888-394-7377.
To report adverse events, call 1-877-737-7226.
For medical information, call 1-800-739-0565.

June 2009

900874R05

TRADE CARTON - PRINCIPAL DISPLAY PANEL - 45 MCG 200 ACTUATIONS

NDC 54868-5689-0

Xopenex HFA®

(levalbuterol tartrate)

Inhalation Aerosol

45 mcg / actuation

200 Metered Inhalations

FOR ORAL INHALATION WITH Xopenex HFA® ACTUATOR ONLY

Shake well before using.

Rx only

Net Contents 15g

Contains No chlorofluorocarbons (CFCs).